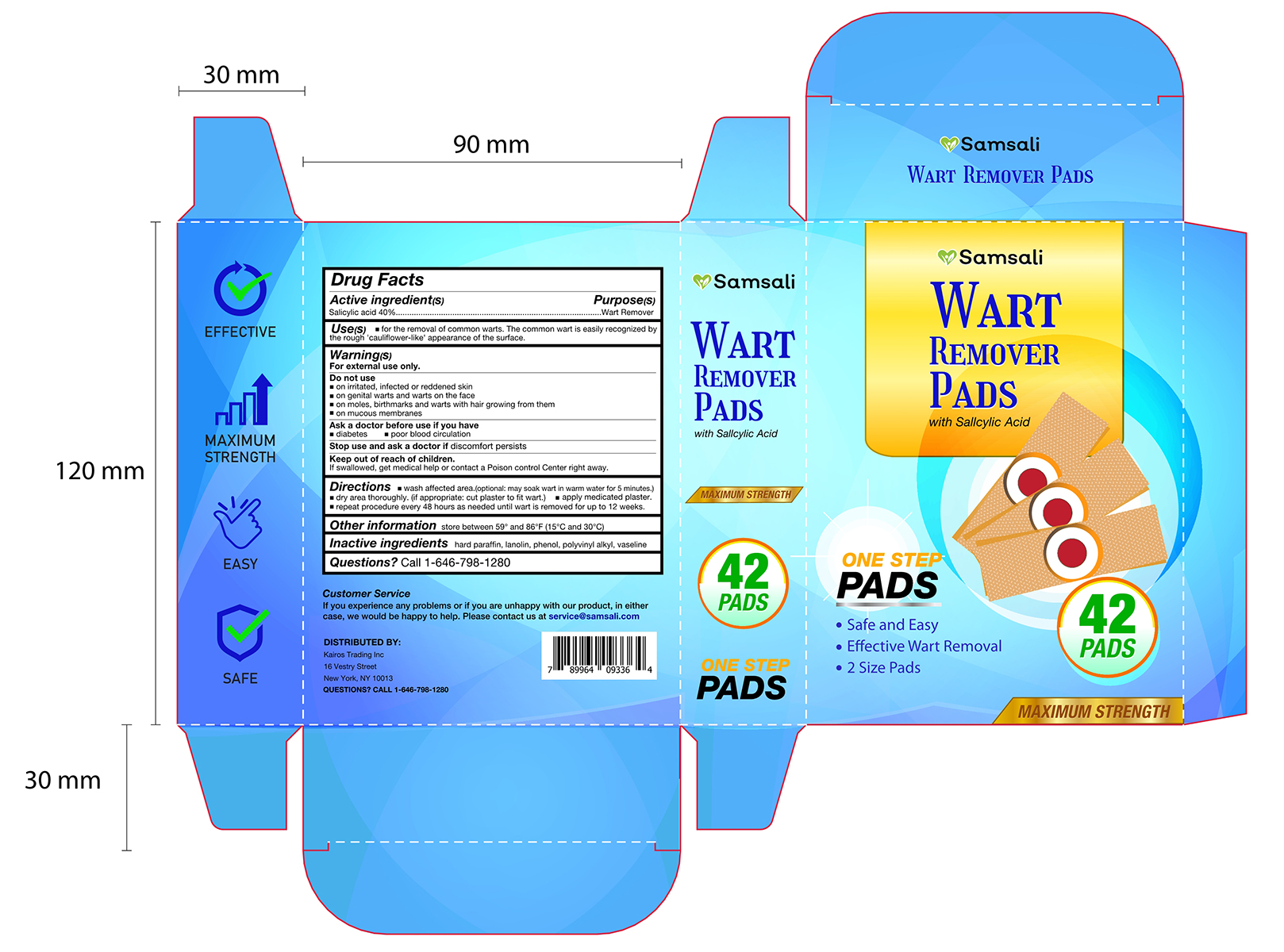 DRUG LABEL: Samsali Wart Remover Pads
NDC: 83124-001 | Form: PATCH
Manufacturer: Kairos Trading Inc
Category: otc | Type: HUMAN OTC DRUG LABEL
Date: 20221124

ACTIVE INGREDIENTS: SALICYLIC ACID 40 g/100 1
INACTIVE INGREDIENTS: LANOLIN; POLYVINYL ACETATE; PETROLATUM; PARAFFIN

83124-001
Samsali Wart Remover Pads

Active ingredient(S)

Salicylic acid 40%

Purpose(s)

Wart Remover

Use(s)

for the removal of common warts. The common wart is easily recognized bythe rough 'cauliflower-like' appearance of the surface.

Warning(S)

Do not use
on irritated, infected or reddened skin
on genital warts and warts on the face
on moles, birthmarks and warts with hair growing from them
on mucous membranes

Ask a doctor before use if you have
diabetes
poor blood circulation

Stop use and ask a doctor if discomfort persists
Keep out of reach of children.
If swallowed, get medical help or contact a Poison control Center right away.

Do not use

on irritated, infected or reddened skin
on genital warts and warts on the face
on moles, birthmarks and warts with hair growing from them
on mucous membranes

Ask a doctor before use if you have

diabetes
poor blood circulation

Stop use and ask a doctor if discomfort persists

Keep out of reach of children.

Directions

wash affected area.(optional: may soak wart in warm water for 5 minutes.
dry area thoroughly. (if appropriate: cut plaster to fit wart)
apply medicated plaster.
repeat procedure every 48 hours as needed unti wart is removed for up to 12 weeks.

Other information

store between 59° and 86°F(15°C and 30°C)

Inactive ingredients

hard paraffin, lanolin, phenol, polyvinyl alkyl, vaseline

Questions?

Call 1-646-798-1280

Package Label

42 PATCH in 1 BOX 83124-001-01